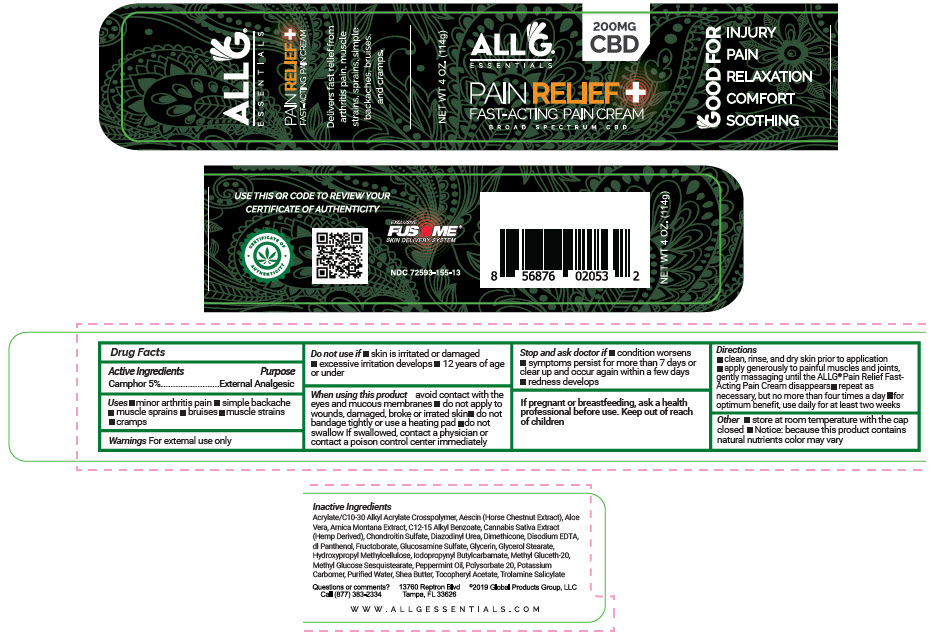 DRUG LABEL: AllG Pain Relief 
NDC: 72593-155 | Form: CREAM
Manufacturer: Global Products Group, LLC
Category: otc | Type: HUMAN OTC DRUG LABEL
Date: 20220124

ACTIVE INGREDIENTS: CAMPHOR (SYNTHETIC) 5 mg/100 g
INACTIVE INGREDIENTS: Methyl Glucose Sesquistearate; CARBOMER INTERPOLYMER TYPE A (ALLYL SUCROSE CROSSLINKED); Alkyl (C12-15) Benzoate; ALOE VERA LEAF; ARNICA MONTANA WHOLE; CALCITRIOL; CHONDROITIN SULFATE (SHARK); Diazolidinyl Urea; Iodopropynyl Butylcarbamate; Dimethicone; EDETATE DISODIUM ANHYDROUS; PANTHENOL; .ALPHA.-TOCOPHEROL ACETATE; Escin; GLUCOSAMINE SULFATE POTASSIUM CHLORIDE; Glycerin; GLYCERYL MONOSTEARATE; HYPROMELLOSE, UNSPECIFIED; Methyl Gluceth-20; Peppermint Oil; Potassium Hydroxide; WATER; Shea Butter; Sorbitan Monolaurate; Trolamine Salicylate; Cannabidiol

AllG® Pain Relief
Fast Acting Pain Cream

Drug Facts

Active Ingredients

Camphor 5%

Purpose

External Analgesic

Uses

- minor arthritis pain
- simple backache
- muscle sprains
- bruises
- muscle strains
- cramps

Warnings

For external use only

Do not use if

- skin is irritated or damaged
- excessive irritation develops
- 12 years of age or under

When using this product avoid contact with the eyes and mucous membranes

- do not apply to wounds, damaged, broke or irrated skin
- do not bandage tightly or use a heating pad
- do not swallow If swallowed, contact a physician or contact a poison control center immediately

Stop and ask doctor if

- condition worsens
- symptoms persist for more than 7 days or clear up and occur again within a few days
- redness develops

PREGNANCY OR BREAST FEEDING

If pregnant or breastfeeding, ask a health professional before use.

Keep out of reach of children

Directions

- clean, rinse, and dry skin prior to application
- apply generously to painful muscles and joints, gently massaging until the ALLG® Pain Relief Fast- Acting Pain Cream disappears
- repeat as necessary, but no more than four times a day
- for optimum benefit, use daily for at least two weeks

Other

- store at room temperature with the cap closed
- Notice: because this product contains natural nutrients color may vary

Inactive Ingredients

Acrylate/C10-30 Alkyl Acrylate Crosspolymer, Aescin (Horse Chestnut Extract), Aloe Vera, Arnica Montana Extract, C12-15 Alkyl Benzoate, Cannabis Sativa Extract (Hemp Derived), Chondroitin Sulfate, Diazodinyl Urea, Dimethicone, Disodium EDTA, dl Panthenol, Fructoborate, Glucosamine Sulfate, Glycerin, Glycerol Stearate, Hydroxypropyl Methylcellulose, Iodopropynyl Butylcarbamate, Methyl Gluceth-20, Methyl Glucose Sesquistearate, Peppermint Oil, Polysorbate 20, Potassium Carbomer, Purified Water, Shea Butter, Tocopheryl Acetate, Trolamine Salicylate

Questions or comments?

Call (877) 383-2334

PRINCIPAL DISPLAY PANEL - 114 g Jar Label

NET WT 4 OZ. (114g)

ALL G®
ESSENTIALS
200MG
CBD

PAIN RELIEF +
FAST-ACTING PAIN CREAM
BROAD SPECTRUM CBD

GOOD FOR
INJURY
PAIN
RELAXATION
COMFORT
SOOTHING